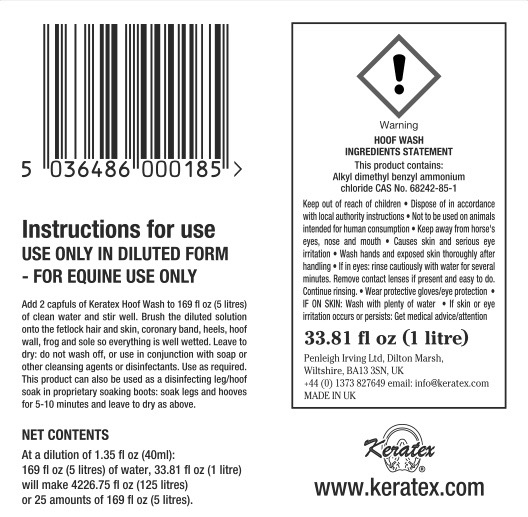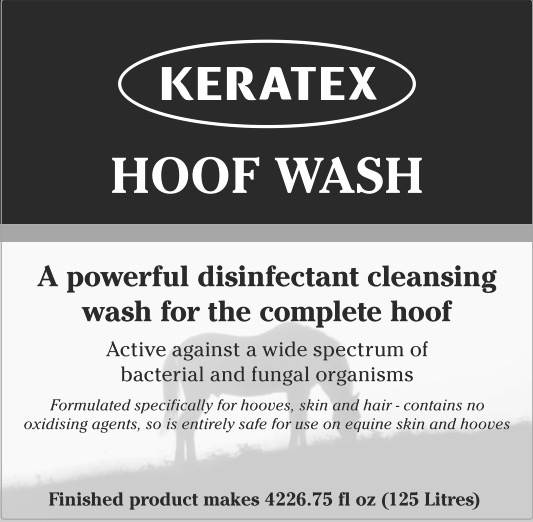 DRUG LABEL: Keratex
NDC: 27426-012 | Form: LIQUID
Manufacturer: Penleigh Irving Ltd
Category: animal | Type: OTC ANIMAL DRUG LABEL
Date: 20190102

ACTIVE INGREDIENTS: BENZALKONIUM 25.6 g/1 L

Keep out of reach of children. Dispose of in accordance with local authority instructions. Not to be used on animals intended for human consumption. Keep away from horse's eyes, nose and mouth. Causes skin and serious eye irritation. Wash hands and exposed skin thoroughly after handling. If in eyes: rinse cautiously with water for several minutes. Remove contact lenses if present and easy to do. Continue rinsing. Wear protective gloves/eye protection. IF ON SKIN: Wash with plenty of water. If skin or eye irritation occurs or persists: Get medical advice/attention.

PACKAGE LABEL

Keratex Hoof Wash

A powerful disinfectant cleansing wash for the complete hoof

Active against a wide spectrum of bacterial and fungal organisms

Formulated specifically for hooves, skin and hair – contains no oxidizing agents, so it is entirely safe for use on equine skin and hooves

Instructions for use. Use only in diluted form – For equine use only

Add two capfuls of Keratex Hoof Wash to 169 fl oz (5 liters) of clean water and stir well. Brush the diluted solution onto the fetlock hair and skin, coronary band, heels, hoof wall, frog & sole so everything is well wetted. Leave to dry: do not wash off, or use in conjunction with soap or other cleansing agents or disinfectants. Use as required. This product can also be used as a disinfecting leg/hoof soak in proprietary soaking boots: soak legs and hooves for 5-10 minutes and leave to dry as above.

Hoof Wash Ingredients Statement: This product contains: Alkyl dimethyl benzyl ammonium chloride CAS No. 68424-85-1.

Finished products makes 4226.75 fl oz (125 Liters)

At a dilution of 40ml: 5 litres of water. 1 Litre will make 125 litres or 25 treatments of 5 litres.

Net Contents. At a dilution of 1.35 fl oz (40ml): 169 fl oz (5 liters) of water, 33.81 fl oz (1 litre) will make 4226.74 fl oz (125 litres) or 25 amounts of 169 flo oz (5 litres).

33.81 fl oz (1 liter)

Penleigh Irving Ltd.

Dilton Marsh, Wiltshire, BK13 3SN, UK

+44 (0) 1373 827649 email: info@keratex.com

www.keratex.com

MADE IN UK